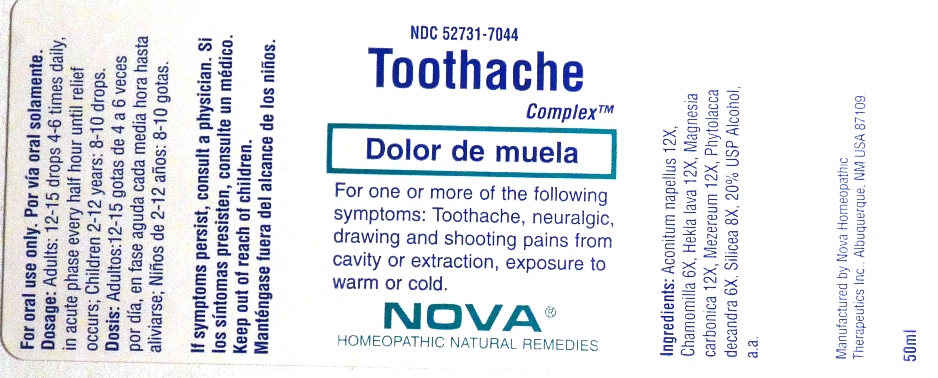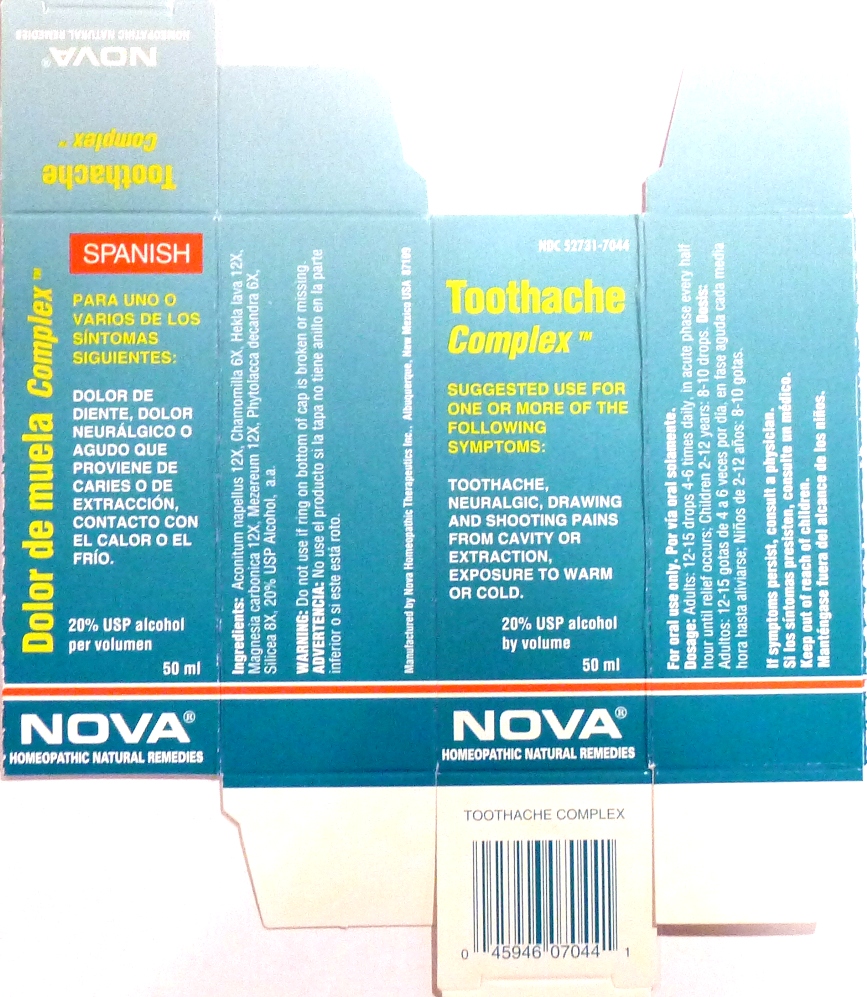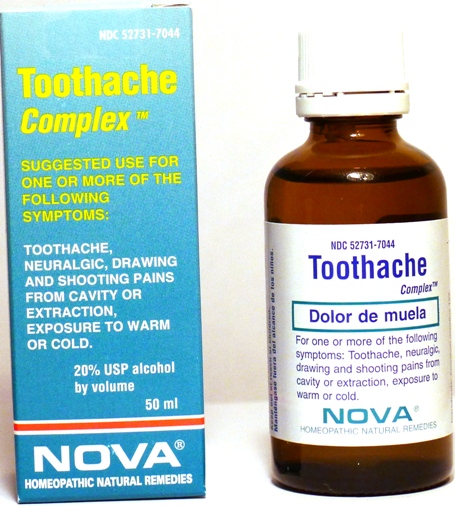 DRUG LABEL: Toothache Complex
NDC: 52731-7044 | Form: LIQUID
Manufacturer: Nova Homeopathic Therapeutics, Inc.
Category: homeopathic | Type: HUMAN OTC DRUG LABEL
Date: 20110601

ACTIVE INGREDIENTS: ACONITUM NAPELLUS 12 [hp_X]/1 mL; MATRICARIA RECUTITA 6 [hp_X]/1 mL; HEKLA LAVA 12 [hp_X]/1 mL; MAGNESIUM CARBONATE 12 [hp_X]/1 mL; DAPHNE MEZEREUM BARK 12 [hp_X]/1 mL; PHYTOLACCA AMERICANA ROOT 6 [hp_X]/1 mL; SILICON DIOXIDE 8 [hp_X]/1 mL
INACTIVE INGREDIENTS: ALCOHOL

Toothache Complex

Purpose:

Suggested use for one or more of the following symptoms:

Toothache, neuralgic, drawing and shooting pains from cavity or extraction, exposure to warm or cold.

Usage and Dosage:

For oral use only.

DOSAGE AND ADMINISTRATION

Adults:
In Acute Phase:
12-15 drops, every half hour until relief occurs
When Relief Occurs:
12-15 drops, 4-6 times per day
Children 2-12 years:
8-10 drops, 4-6 times per day

Warnings:

Keep out of reach of children.

WARNINGS

If symptoms persist, consult a physician.
Do not use if ring on bottom of cap is broken or missing.

Active Ingredients:

Aconitum napellus 12X, Chamomilla 6X, Hekla lava 12X, Magnesia carbonica 12X, Mezereum 12X, Phytolacca decandra 6X, Silicea 8X

Inactive Ingredients:

Alcohol, 20% USP

QUESTIONS

Manufactured by Nova Homeopathic Therapeutics Inc., Albuquerque, New Mexico USA 87109
1-800-225-8094

PACKAGE LABEL

Toothache Complex Product

Toothache Complex Bottle Label

Toothache Complex Box